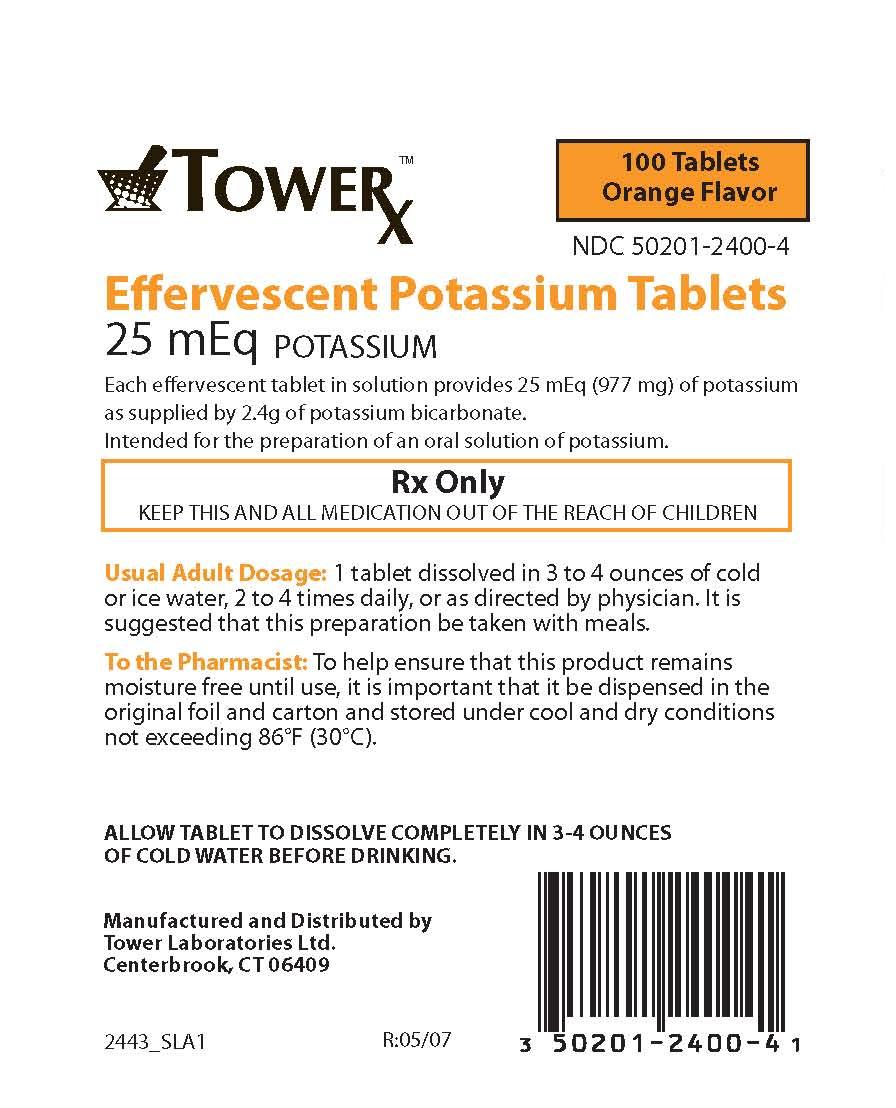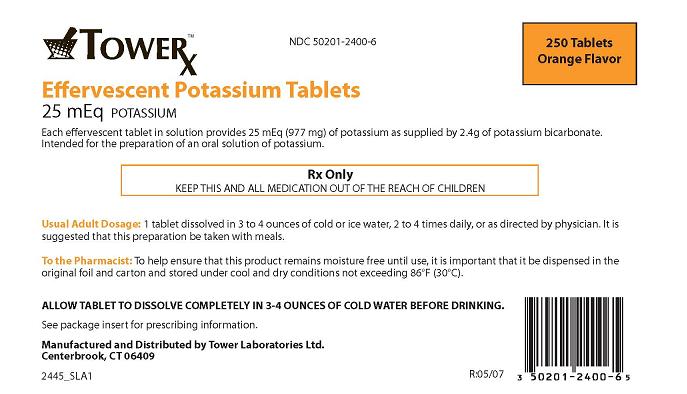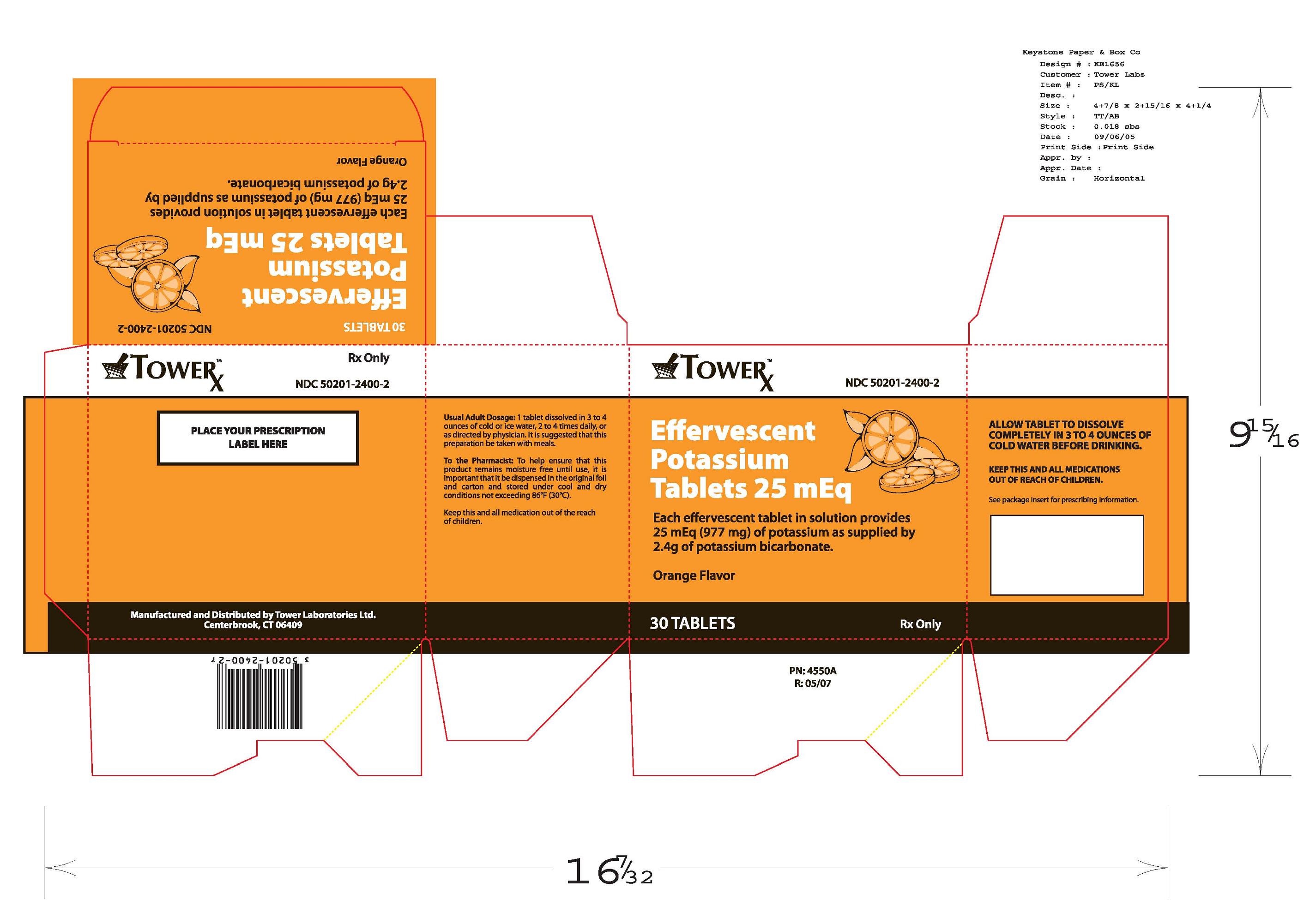 DRUG LABEL: TowerX Effervescent Potassium 
NDC: 50201-2400 | Form: TABLET, EFFERVESCENT
Manufacturer: Tower Laboratories Ltd
Category: prescription | Type: HUMAN PRESCRIPTION DRUG LABEL
Date: 20101214

ACTIVE INGREDIENTS: POTASSIUM BICARBONATE 25 meq/1 1
INACTIVE INGREDIENTS: SORBITOL 0.971 g/1 1; CITRIC ACID 1.4 g/1 1; SACCHARIN SODIUM ANHYDROUS 0.039 g/1 1; POLYETHYLENE GLYCOL 8000 0.103 g/1 1; SODIUM BENZOATE 0.077 g/1 1

PACKAGE INSERT

DESCRIPTION: An oral potassium supplement. Each effervescent tablet in solution provides 25 mEq of potassium as supplied by 2.4g potassium bicarbonate with 1.4g Citric Acid, FD and C Yellow #6 Dye, FD and C Yellow #6 Lake, Natural Orange Flavor, Polyethylene Glycol, Saccharin, Sodium Benzoate, and Sorbitol.

CLINICAL PHARMACOLOGY

CLINICAL PHARMACOLOGY: Potassium ion is the principal intracellular cation of most body tissues. Potassium ions participate in many essential physiological processes, such as the maintenance of intracellular tonicity, nerve impulse transmission, enzymatic reactions in intermediary metabolism, cardiac, skeletal and smooth muscle function, and the maintenance of normal renal function.

Potassium depletion may occur whenever the rate of potassium loss through renal excretion and/or loss from the gastrointestinal tract exceeds the rate of potassium intake. Potassium depletion usually develops slowly as a result of lengthy therapy with oral diuretics, primary or secondary hyperaldosteronism, diabetic ketoacidosis, or inadequate replacement of potassium in patients on prolonged parenteral nutrition. Depletion is additionally associated with severe diarrhea, accompanied by vomiting. Potassium depletion due to these causes is usually accompanied by a concomitant loss of chloride and is manifested by hypokalemia and metabolic alkalosis. Potassium depletion may result in fatigue, weakness, nausea, drowsiness, loss of appetite, edema, oliguria and chronic ileus with distention. Potassium deficiency may be manifested by shallow breathing, lowered blood pressure, disturbances of cardiac rhythm (primarily ectopic beats), prominent U-waves in the electrocardiogram, or other ECG changes, such as lengthened Q-T interval, depressed S-T segment, and depressed or inverted T-wave. In advanced cases of potassium deficiency, flaccid paralysis and/or impaired ability to concentrate urine may be evident.

INDICATIONS AN USAGE:
1. For therapeutic use in patients with hypokalemia with or without metabolic alkalosis; in digitalis intoxication and in patients with hypokalemic familial
periodic paralysis.
2. For prevention of potassium depletion when the dietary intake of potassium is inadequate in the following conditions; patients receiving digitalis and
diuretics for congestive heart failure; hepatic cirrhosis with ascites; states of aldosterone excess with normal renal function; potassium-losing
nephropathy, and certain diarrheal states.
3. The use of potassium salts in patients receiving diuretics for uncomplicated essential hypertension is often unnecessary when such patients have a
normal dietary pattern. Serum potassium should be checked periodically, however, and, if hypokalemia occurs, dietary supplementation with
potassium-containing foods may be adequate to control milder cases. In more severe cases supplementation with potassium salts may be
indicated.

CONTRAINDICATIONS

CONTRAINDICATIONS: Potassium supplements are contraindicated for patients having hyperkalemia, since a further increase in serum potassium level in these patients can results in cardiac arrest. Hyperkalemia may complicate any of the following conditions;chronic renal failure; systemic acidosis, such as diabetic acidosis, acute dehydration; extensive tissue breakdown, as in severe burns; adrenal insufficiency. Hypokalemia should not be treated by the simultaneous use of potassium salts and a potassium sparing diuretic, such as spironolactone or triamterene, since the concomitant use of these medications can result in severe hyperkalmia.

WARNINGS

WARNINGS: The administration of potassium salts can produce hyperkalemia and cardiac arrest in patients with impaired mechanisms for potassium excretion. These reactions most commonly occur in patients receiving potassium intravenously, but may also occur in patients receiving oral potassium. Potentially fatal hyperkalemia can develop quickly and be asymptomatic. Patients using potassium salts with chronic renal disease, or any other condition which impairs the excretion of potassium, require especially careful monitoring of serum potassium concentration and appropriate adjustment of dosage.

PRECAUTIONS

PRECAUTIONS: General Precautions - The diagnosis of potassium depletion is ordinarily made by demonstrating hypokalemia in a patient with a clinical history suggesting a cause for potassium depletion. When interpreting the serum potassium concentration, the physician should be aware that acute alkalosis can cause hypokalemia without showing a deficit in total body potassium. Acute acidosis can increase the serum potassium level to normal even with a reduced total body potassium.. Thus close attention to acid-base balance, serum electrolytes, the clinical status of the patient, and the ECG is required in the treatment of potassium depletion.

PATIENT COUNSELING INFORMATION

Information for Patients - Patients should be instructed to dissolve each tablet completely in the required amount of water to reduce the risk of gastrointestinal irritation associated with the oral use of concentrated potassium salt products. Patients should not open foil pouch until time of use.

LABORATORY TESTS

Laboratory Tests - Serum potassium determinations and ECG should be part of the frequent clinical evaluation of the patient.

DRUG INTERACTIONS

Drug Interactions - Severe hyperkalemia can be produced by the simultaneous administration of potassium supplements and a potassium-sparing diuretic (see Contraindications). Potassium supplements should be used carefully by patients who are using salt substitutes, because many of these substitutes contain large amounts of potassium. This simultaneous use could produce hyperkalemia.

PREGNANCY

Usage in Pregnancy - Pregnancy Category C - Animal reproduction studies have not been conducted with this effervescent potassium product. It is unknown whether this product can cause fetal harm when given to a pregnant woman or if it can affect reproductive capacity. Pregnant women should be given this product only if it is clearly needed.

NURSING MOTHERS

Nursing Mothers - Because many drugs are excreted in human milk, there exists the potential for serious adverse reactions in nursing infants from oral potassium supplements. Therefore, it should be decided whether to discontinue nursing or to discontinue the drug, considering the importance of the drug to the mother.

PEDIATRIC USE

Pediatric Use - Safety and effectiveness in children have not been established.

ADVERSE REACTIONS

ADVERSE REACTIONS: Abdominal discomfort, diarrhea, vomiting, and nausea are the most common adverse reactions tooral potassium supplements. These adverse reactions occur most frequently when the preparation is not taken with food, is not properly diluted, or not completely dissolved.
Hyperkalemia occurs infrequently in patients with normal renal function who receive oral potassium supplements. The following are symptoms of hyperkalemia: mental confusion, unexplained anxiety, cardiac arrhythmias, numbness or tingling in lips, feet, or hands, difficult breathing or shortness of breath, weakness or heaviness of legs, and unusual fatigue or weakness. (See Contraindications, Warnings, and Overdosage).

OVERDOSAGE

OVERDOSAGE: The use of oral potassium salts by persons with normal renal functions rarely results in serious hyperkalemia. However, if excretory mechanisms are impaired or if potassium is administered too rapidly intravenously, potentially fatal hyperkalemia can result (See Contraindications and Warnings). The earliest clinical signs of hyperkalemia may be only increased serum potassium concentrations and characteristic ECG changes, such as depression of S-T segment, prolongation of the QT interval, peaking of T-waves and the loss of P-wave. The above mentioned changes in the ECG most frequently occur when the serum potassium level gets to 7 to 8 mEq per liter. At a level of 9 to 10 mEq per liter, other clinical manifestations may occur, such as muscle paralysis and death due to cardiac arrest.
The focus of the treatment of severe hyperkalemia should be on the reduction of the serum potassium level by furthering the transfer of potassium from the extracellular to the intracellular space. The treatment may include the following: a) intravenous administration of 1 liter of a `0 percent glucose solution which contains 20 to 40 units of insulin; b) in the acidolic patient, 150 mEq to 300 mEq of sodium bicarbonate administered intravenously. Other actions should include the discontinuing of potassium-sparing diuretics and potassium-containing drugs and often the oral use of a cations exchange resin (such as sodium polystyrene sulfonate) in order to eliminate gastrointestinal potassium. To make sure that the resin moves rapidly through the gastrointestinal tract, a nonabsorbable polyhydric alcohol such as sorbitol should be administered in sufficient amounts to cause a soft to semiliquid bowel movement to occur every few hours.
Hemodialysis can also be used as an effective alternative means to remove excess potassium.

DOSAGE AND ADMINISTRATION: Adults - One effervescent tablet (25 mEq potassium) completely dissolved in three to four ounces or more of cold water and taken two to four times daily, or as directed by physician. It is suggested this potassium solution be taken with meals and sipped slowly over a five to ten minute period. Do not open foil pouch until time of use.

HOW SUPPLIED

Boxes of 30, 100, and 250 tablets.